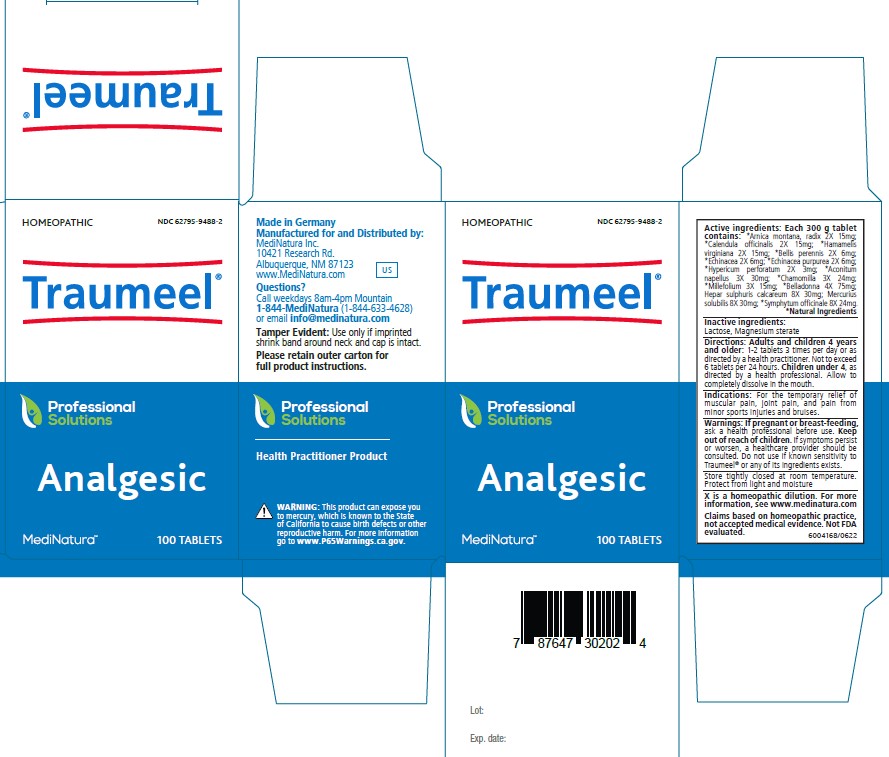 DRUG LABEL: Traumeel
NDC: 62795-9488 | Form: TABLET
Manufacturer: MediNatura Inc
Category: homeopathic | Type: HUMAN OTC DRUG LABEL
Date: 20230926

ACTIVE INGREDIENTS: ATROPA BELLADONNA 4 [hp_X]/1 1; ECHINACEA, UNSPECIFIED 2 [hp_X]/1 1; ACONITUM NAPELLUS 3 [hp_X]/1 1; ARNICA MONTANA ROOT 2 [hp_X]/1 1; BELLIS PERENNIS 2 [hp_X]/1 1; CALENDULA OFFICINALIS FLOWERING TOP 2 [hp_X]/1 1; CALCIUM SULFIDE 8 [hp_X]/1 1; HYPERICUM PERFORATUM 2 [hp_X]/1 1; COMFREY ROOT 8 [hp_X]/1 1; MATRICARIA RECUTITA 3 [hp_X]/1 1; HAMAMELIS VIRGINIANA LEAF 2 [hp_X]/1 1; ECHINACEA PURPUREA 2 [hp_X]/1 1; MERCURIUS SOLUBILIS 8 [hp_X]/1 1; ACHILLEA MILLEFOLIUM 3 [hp_X]/1 1
INACTIVE INGREDIENTS: LACTOSE, UNSPECIFIED FORM; MAGNESIUM STEARATE

Traumeel

Indications:

For the temporary relief of
muscular pain, joint pain, and pain from
minor sports injuries and bruises.

Warnings:

If pregnant or breast-feeding,
ask a health professional before use. Keep
out of reach of children. If symptoms persist
or worsen, a healthcare provider should be
consulted. Do not use if known sensitivity to
Traumeel® or any of its ingredients exists

Directions:

Adults and children 4 years
and older: 1-2 tablets 3 times per day or as
directed by a health practitioner. Not to exceed
6 tablets per 24 hours. Children under 4, as
directed by a health professional. Allow to
completely dissolve in the mouth.

Inactive ingredients:

Lactose, Magnesium sterate

KEEP OUT OF REACH OF CHILDREN

Purpose

Analgesic

Active ingredients:

Each 300 g tablet
contains: *Arnica montana, radix 2X 15mg;
*Calendula officinalis 2X 15mg; *Hamamelis
virginiana 2X 15mg; *Bellis perennis 2X 6mg;
*Echinacea 2X 6mg; *Echinacea purpurea 2X 6mg;
*Hypericum perforatum 2X 3mg; *Aconitum
napellus 3X 30mg; *Chamomilla 3X 24mg;
*Millefolium 3X 15mg; *Belladonna 4X 75mg;
Hepar sulphuris calcareum 8X 30mg; Mercurius
solubilis 8X 30mg; *Symphytum officinale 8X 24mg.
*Natural Ingredients

PACKAGE LABEL

Add image transcription here...